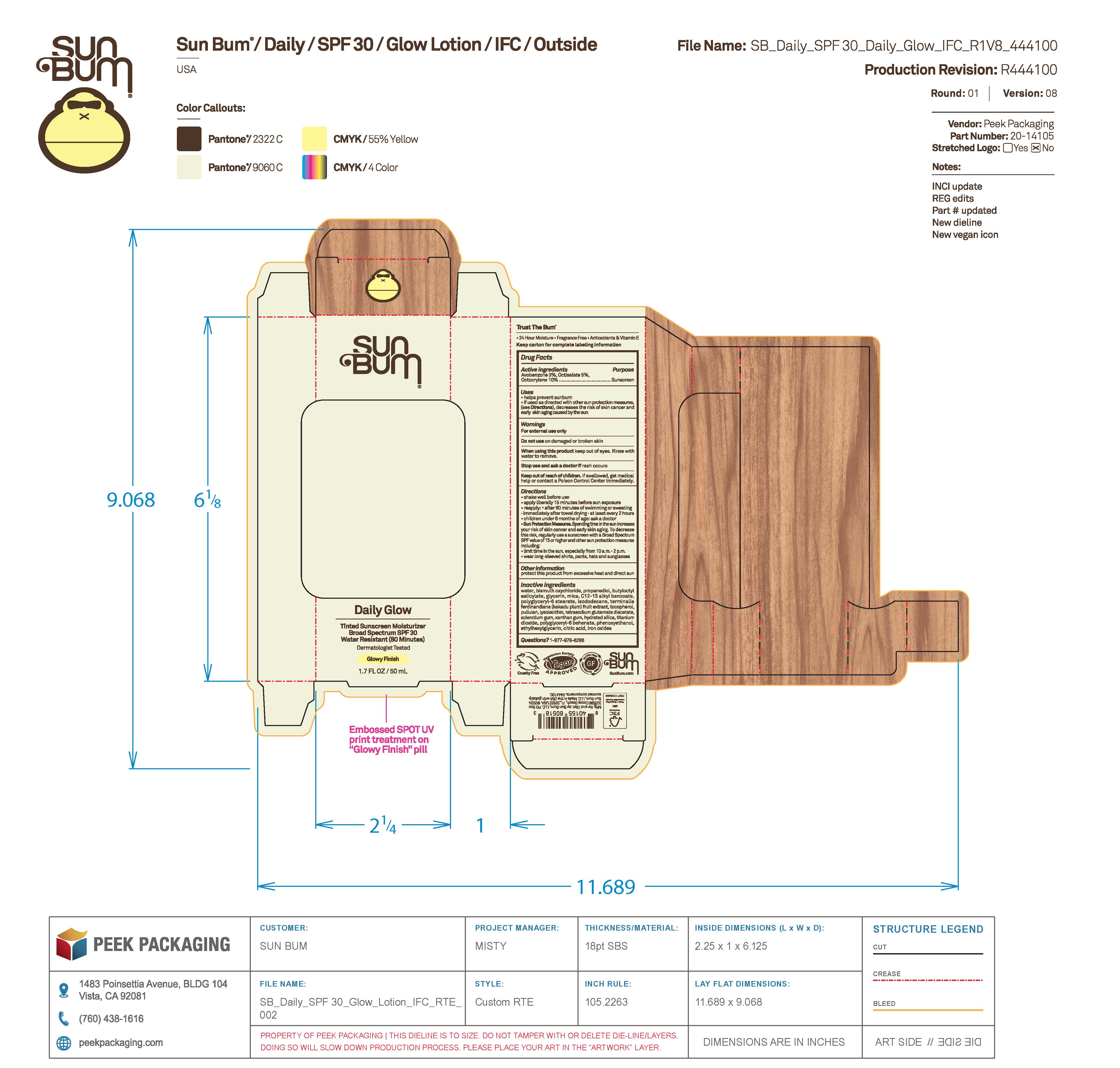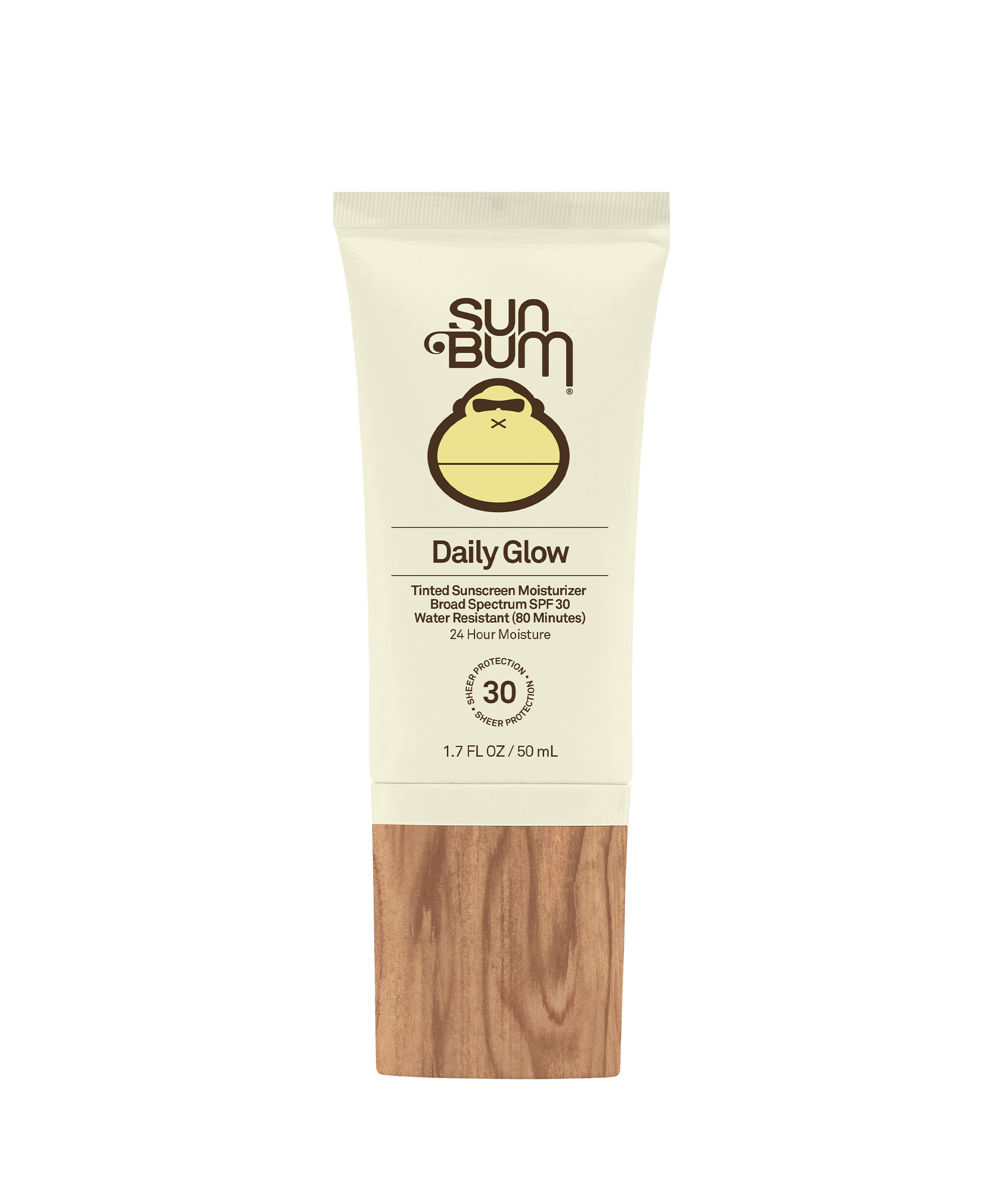 DRUG LABEL: Sun Bum Daily Glow Tinted Sunscreen Moisturizer Broad Spectrum SPF 30
NDC: 69039-668 | Form: LOTION
Manufacturer: Sun Bum, LLC
Category: otc | Type: HUMAN OTC DRUG LABEL
Date: 20250923

ACTIVE INGREDIENTS: AVOBENZONE 30 mg/1 mL; OCTISALATE 50 mg/1 mL; OCTOCRYLENE 100 mg/1 mL
INACTIVE INGREDIENTS: ISODODECANE; HYDRATED SILICA; POLYGLYCERYL-6 BEHENATE; SCLEROTIUM GUM; TITANIUM DIOXIDE; MICA; XANTHAN GUM; PHENOXYETHANOL; PROPANEDIOL; BUTYLOCTYL SALICYLATE; ETHYLHEXYLGLYCERIN; C12-15 ALKYL BENZOATE; KAKADU PLUM; FERRIC OXIDE RED; WATER; LYSOPHOSPHATIDYLCHOLINE, SOYBEAN; BISMUTH OXYCHLORIDE; PULLULAN; POLYGLYCERYL-6 STEARATE; GLYCERIN; TOCOPHEROL; TETRASODIUM GLUTAMATE DIACETATE; CITRIC ACID

Sun Bum Daily Glow Tinted Sunscreen Moisturizer Broad Spectrum SPF 30

Active ingredients:

Avobenzone 3%, Octisalate 5%, Octocrylene 10%

Purpose

Sunscreen

Uses

• helps prevent sunburn • if used as directed with other sun protection measures, (see Directions) decreases the risk of skin cancer and early skin aging caused by the sun

Warnings

For external use only

Do not use on damaged or broken skin

When using this product keep out of eyes. Rinse with water to remove.

Stop use and ask a doctor if rash occurs

Keep out of reach of children. If swallowed, get medical help or contact a Poison Control Center immediately.

Warnings

Keep Out Of Reach Of Children

Directions

• shake well before use

• apply liberally 15 minutes before sun exposure

• reapply: • after 80 minutes of swimming or sweating • immediately after towel drying • at least every 2 hours

• children under 6 months of age: ask a doctor

• Sun Protection Measures. Spending time in the sun increases your risk of skin cancer and early skin aging. To decrease this risk, regularly use a sunscreen with a Broad Spectrum SPF value of 15 or higher and other sun protection measures including:

• limit time in the sun, especially from 10 a.m.- 2 p.m.

• wear long-sleeved shirts, pants, hats and sunglasses

Directions

• shake well before use

• apply liberally 15 minutes before sun exposure

Other information

protect this product from excessive heat and direct sun

Inactive ingredients

water, bismuth oxychloride, propanediol, butyloctyl salicylate, glycerin, mica, C12-15 alkyl benzoate, polyglyceryl-6 stearate, isododecane, terminalia ferdinandiana (kakadu plum) fruit extract, tocopherol, pullulan, lysolecithin, tetrasodium glutamate diacetate, sclerotium gum, xanthan gum, hydrated silica, titanium dioxide, polyglyceryl-6 behenate, phenoxyethanol, ethylhexylglycerin, citric acid, iron oxides

Questions

Questions? 1-877-978-6286